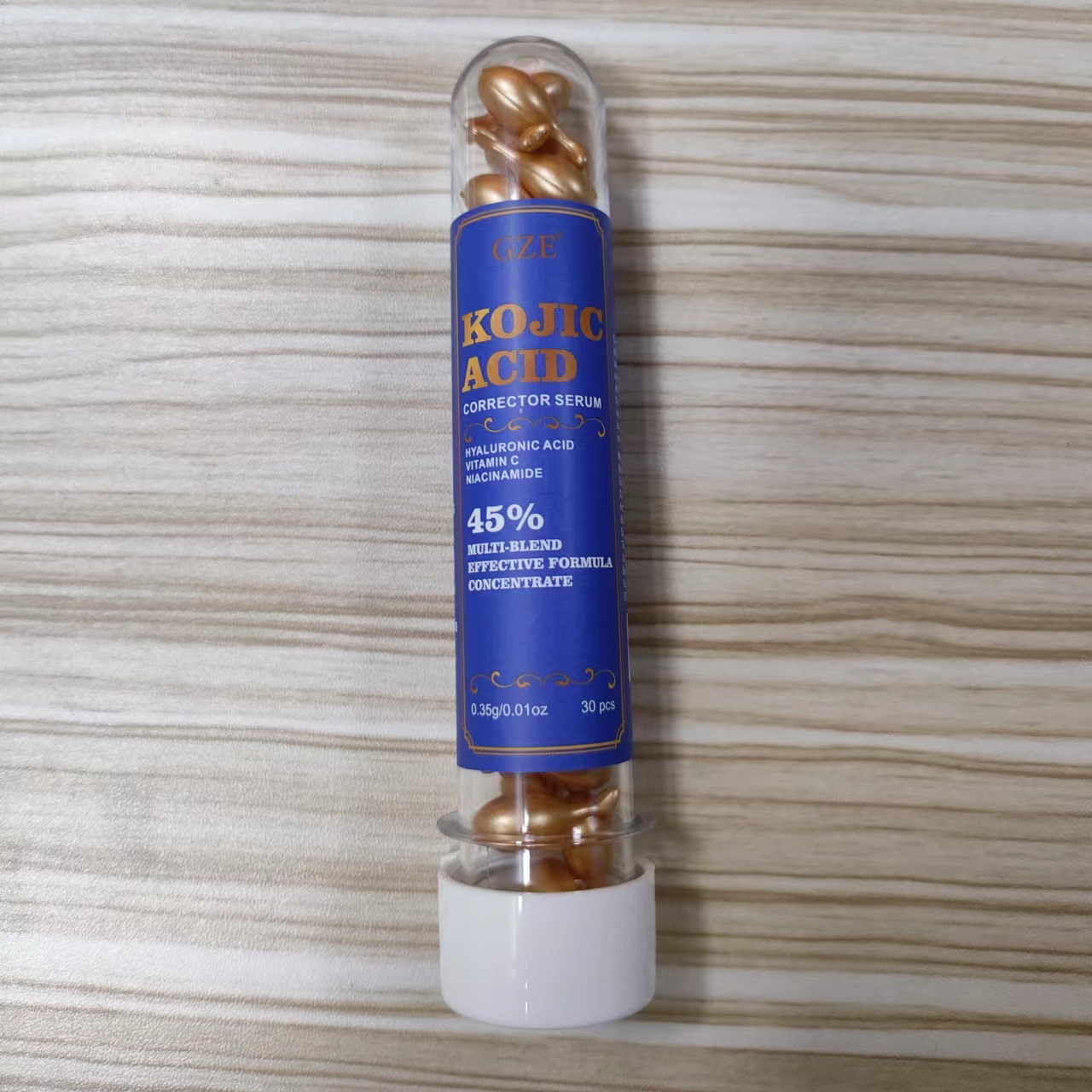 DRUG LABEL: GZE KOJIC ACID CORRECTOR SERUM
NDC: 74458-315 | Form: CAPSULE
Manufacturer: Guangzhou Yilong Cosmetics Co., Ltd
Category: otc | Type: HUMAN OTC DRUG LABEL
Date: 20241228

ACTIVE INGREDIENTS: KOJIC ACID 1.3 g/100 g; ARBUTIN 1.5 g/100 g; NIACINAMIDE 3 g/100 g
INACTIVE INGREDIENTS: ASCORBIC ACID; AQUA; SODIUM HYALURONATE; GLYCYRRHIZA GLABRA (LICORICE) ROOT; .ALPHA.-TOCOPHEROL ACETATE; GLYCERIN

GZE KOJIC ACID CORRECTOR SERUM

ACTIVE INGREDIENT

Kojic Acid

Niacinamide

Arbutin

INACTIVE INGREDIENT

Aqua

Glycerin

Glycyrrhiza Glabra (Licorice) Root Extract

Tocopheryl Acetate

Ascorbic Acid

Sodium Hyaluronate

PURPOSE

Whitening.

INDICATIONS AND USAGE

Apply 1-2 capsules of Dark Spot Serum
onto clean skin and gently massage in. Use morning and night
for best results. Avoid contact with eyes

WARNINGS

For external use only.

Stop use and ask a doctor if rash occurs.

DO NOT USE

1. Do not use on damaged or broken skin.

When using this product keep out of eyes. Rinse with water to remove.

Keep out of reach of children. If swallowed, get medical help or contact a Poison Control Center right away.

DOSAGE AND ADMINISTRATION

Apply 1-2 capsules of Dark Spot Serum
onto clean skin and gently massage in. Use morning and night
for best results. Avoid contact with eyes